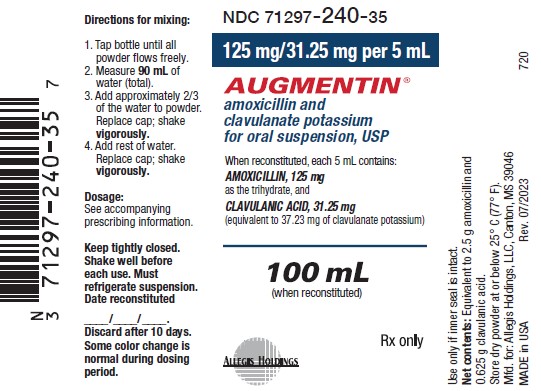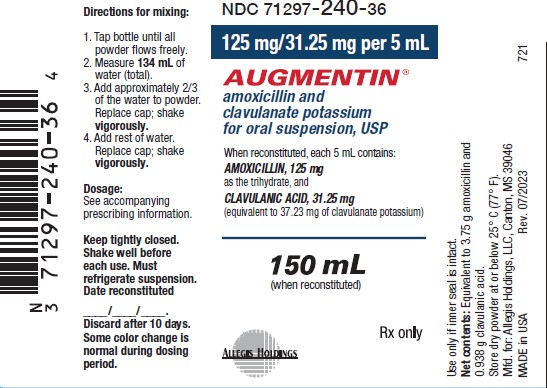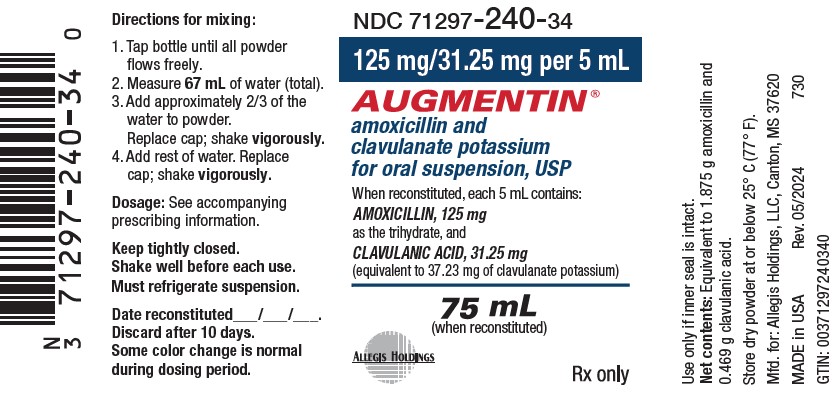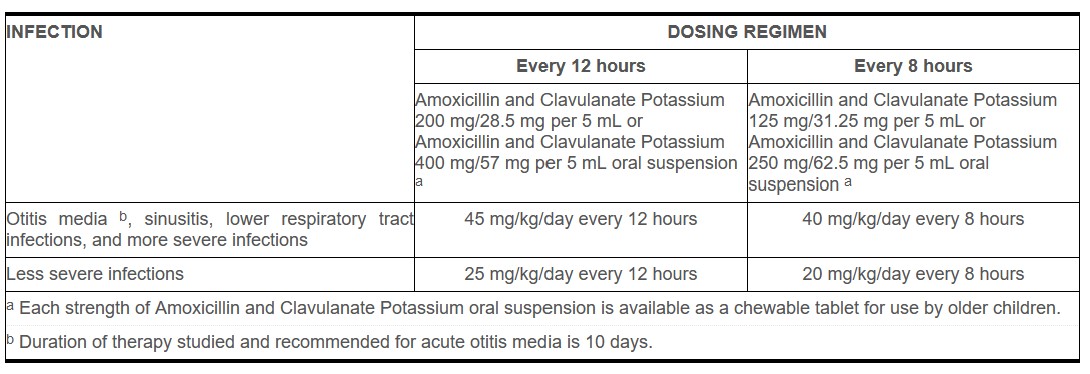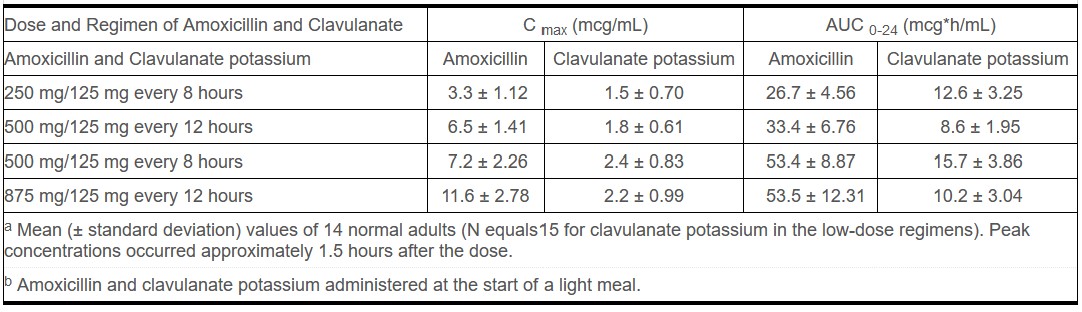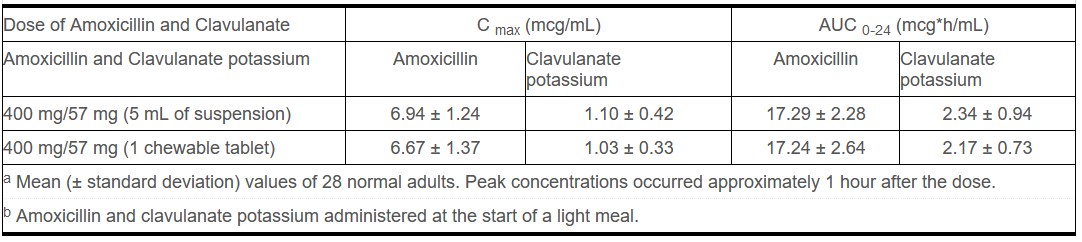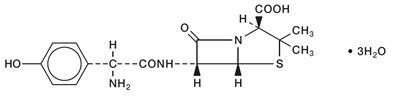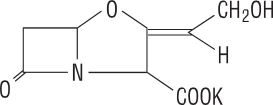 DRUG LABEL: Augmentin
NDC: 71297-240 | Form: FOR SUSPENSION
Manufacturer: Allegis Holdings, LLC
Category: prescription | Type: HUMAN PRESCRIPTION DRUG LABEL
Date: 20240516

ACTIVE INGREDIENTS: AMOXICILLIN 125 mg/5 mL; CLAVULANATE POTASSIUM 31.25 mg/5 mL
INACTIVE INGREDIENTS: SILICON DIOXIDE; XANTHAN GUM; MANNITOL; SUCCINIC ACID; SACCHARIN SODIUM

HIGHLIGHTS OF PRESCRIBING INFORMATION

These highlights do not include all the information needed to use AUGMENTIN safely and effectively. See full prescribing information for AUGMENTIN.
Augmentin (amoxicillin and clavulanate potassium) for oral suspension
Initial U.S. Approval: 1984

1 INDICATIONS AND USAGE

AUGMENTIN is a combination of amoxicillin, a penicillin-class antibacterial and clavulanate potassium, a beta‑lactamase inhibitor indicated for treatment of the following infections in adults and pediatric patients: (1)

- Lower respiratory tract infections
- Acute bacterial otitis media
- Sinusitis
- Skin and skin structure infections
- Urinary tract infections

Limitations of Use

When susceptibility test results show susceptibility to amoxicillin, indicating no beta-lactamase production, AUGMENTIN should not be used. (1)

Usage

To reduce the development of drug-resistant bacteria and maintain the effectiveness of AUGMENTIN and other antibacterial drugs, AUGMENTIN should be used only to treat or prevent infections that are proven or strongly suspected to be caused by bacteria. (1)

2 DOSAGE AND ADMINISTRATION

- Adults and Pediatric Patients greater than 40 kg: 500 or 875 mg every 12 hours or 250 or 500 mg every 8 hours, based on the amoxicillin component. (2.2, 2.3)
- Pediatric patients aged 12 weeks (3 months) and older: 25 to 45 mg/kg/day every 12 hours or 20 to 40 mg/kg/day every 8 hours, up to the adult dose. (2.3)
- Neonates and infants less than 12 weeks of age: 30 mg/kg/day divided every 12 hours, based on the amoxicillin component. Use of the 125 mg/5 mL oral suspension is recommended. (2.3)

3 DOSAGE FORMS AND STRENGTHS

- For Oral Suspension: 125 mg/31.25 mg per 5 mL, 250 mg/62.5 mg per 5 mL (3)

4 CONTRAINDICATIONS

- History of a serious hypersensitivity reaction (e.g., anaphylaxis or Stevens-Johnson syndrome) to AUGMENTIN or to other beta‑lactams (e.g., penicillins or cephalosporins). (4.1)
- History of cholestatic jaundice/hepatic dysfunction associated with AUGMENTIN. (4.2)

5 WARNINGS AND PRECAUTIONS

- Serious (including fatal) hypersensitivity reactions: Discontinue AUGMENTIN if a reaction occurs. (5.1)
- Severe Cutaneous Adverse Reactions (SCAR): Monitor closely. Discontinue if rash progresses. (5.2)
- Drug-induced enterocolitis syndrome (DIES) has been reported with use of Amoxicillin, A componet of Augmentin. If this occures, discontinue AUGMENIN and institute appropriate therapy (5.3)
- Hepatic dysfunction and cholestatic jaundice: Discontinue if signs/symptoms of hepatitis occur. Monitor liver function tests in patients with hepatic impairment. (5.4)
- Clostridioides difficile-associated diarrhea (CDAD): Evaluate patients if diarrhea occurs. (5.5)
- Patients with mononucleosis who receive AUGMENTIN develop skin rash. Avoid AUGMENTIN use in these patients. (5.6
- Overgrowth: The possibility of superinfections with fungal or bacterial pathogens should be considered during therapy. (5.7)

6 ADVERSE REACTIONS

5.4The most frequently reported adverse effects were diarrhea/loose stools (9%), nausea (3%), skin rashes and urticaria (3%), vomiting (1%) and vaginitis (1%). (6.1)

To report SUSPECTED ADVERSE REACTIONS, contact Allegis Holdings, LLC at 1-866-633-9033 or FDA at 1-800-FDA-1088 or www.fda.gov/medwatch.

7 DRUG INTERACTIONS

- Co‑administration with probenecid is not recommended. (7.1)
- Concomitant use of AUGMENTIN and oral anticoagulants may increase the prolongation of prothrombin time.(7.2)
- Co-administration with allopurinol increases the risk of rash. (7.3)
- AUGMENTIN may reduce efficacy of oral contraceptives. (7.4)

8 USE IN SPECIFIC POPULATIONS

- Pediatric Use: Modify dose in patients 12 weeks or younger. (8.4)
- Renal Impairment: Dosage adjustment is recommended for severe renal impairment (GFR less than 30mL/min). (2.4, 8.6)]

Recent Major Changes

Warnings and Precautions:

Drug-Induced Enterocolities Syndrome (DIES) (5.3)

5/2024

FULL PRESCRIBING INFORMATION

1 INDICATIONS AND USAGE

AUGMENTIN is indicated for the treatment of infections in adults and pediatric patients, due to susceptible isolates of the designated bacteria in the conditions listed below:

- Lower Respiratory Tract Infections - caused by beta‑lactamase–producing isolates of Haemophilus influenzae and Moraxella catarrhalis.
- Acute Bacterial Otitis Media - caused by beta‑lactamase–producing isolates of H. influenzae and M. catarrhalis.
- Sinusitis - caused by beta‑lactamase–producing isolates of H. influenzae and M. catarrhalis.
- Skin and Skin Structure Infections - caused by beta‑lactamase–producing isolates of Staphylococcus aureus, Escherichia coli, and Klebsiella species.
- Urinary Tract Infections - caused by beta‑lactamase–producing isolates of E. coli, Klebsiella species, and Enterobacter species.

Limitations of Use

When susceptibility test results show susceptibility to amoxicillin, indicating no beta-lactamase production, AUGMENTIN should not be used.

Usage

To reduce the development of drug‑resistant bacteria and maintain the effectiveness of AUGMENTIN and other antibacterial drugs, AUGMENTIN should be used only to treat or prevent infections that are proven or strongly suspected to be caused by susceptible bacteria. When culture and susceptibility information are available, they should be considered in selecting or modifying antibacterial therapy. In the absence of such data, local epidemiology and susceptibility patterns may contribute to the empiric selection of therapy.

2 DOSAGE AND ADMINISTRATION

2.1 Important Administration Instructions

AUGMENTIN may be taken without regard to meals; however, absorption of clavulanate potassium is enhanced when AUGMENTIN is administered at the start of a meal. To minimize the potential for gastrointestinal intolerance, AUGMENTIN should be taken at the start of a meal.

2.2 Adult Patients

See dosing regimens of AUGMENTIN (based on the amoxicillin component) provided in Table 1 below.

Table 1. Dosing Regimens of AUGMENTIN in Adult Patients

TYPE OF INFECTION | DOSING REGIMEN OF Amoxicillin and Clavulanate Potassium
Severe infections and infections of the respiratory tract | one 875 mg tableta of AUGMENTIN every 12 hours or one 500 mg tabletb,c of AUGMENTIN every 8 hours
Less severe infections | one 500 mg tabletb,c of AUGMENTIN every 12 hours or one 250 mg tabletd of AUGMENTIN every 8 hours

a Adults who have difficulty swallowing may be given the AUGMENTIN 200 mg/28.5 mg per 5 mL suspension or the AUGMENTIN 400 mg/57 mg per 5 mL suspension may be used in place of the 875 mg/125 mg tablet.

b Adults who have difficulty swallowing may be given the AUGMENTIN 125 mg/31.25 mg per 5 mL or AUGMENTIN 250 mg/62.5 mg per 5 mL suspension in place of the 500 mg/125 mg tablet.

c Two AUGMENTIN 250 mg/125 mg tablets are NOT substitutable with one 500 mg/125 mg AUGMENTIN tablet [see Dosage and Administration (2.6)] .

d AUGMENTIN 250 mg/125 mg tablet is NOT substitutable with AUGMENTIN 250 mg/62.5 mg chewable tablet [see Dosage and Administration (2.6)]

2.3 Pediatric Patients

Based on the amoxicillin component, AUGMENTIN should be dosed as follows:

Neonates and Infants Aged less than 12 weeks (less than 3 months): See dosing regimens of AUGMENTIN provided in Table 2 below.

Table 2: Dosing Regimens of AUGMENTIN in Neonates and Infants Aged Less than 12 Weeks (Less than 3 Months)

PATIENT POPULATION | DOSING REGIMEN
PATIENT POPULATION | AUGMENTIN 125 mg/31.25 mg per 5 mL for oral suspensiona
Neonates and Infants aged less than 12; weeks (less than 3 months) | 30 mg/kg/day every 12 hours

a Experience with the AUGMENTIN 200 mg/28.5 mg per 5 mL formulation in this age group is limited, and thus, use of the AUGMENTIN 125 mg/31.25 mg per 5 mL for oral suspension is recommended.

Patients Aged 12 weeks (3 months) and Older and Weighing Less than 40 kg: See dosing regimens provided in Table 3 below.

The every 12 hour regimen is recommended as it is associated with significantly less diarrhea [see Clinical Studies (14.2)] .
The Amoxicillin and Clavulanate Potassium 200 mg/28.5 mg per 5 mL and Amoxicillin and Clavulanate Potassium 400 mg/57 mg per 5 mL) for oral suspension and Amoxicillin and Clavulanate Potassium 200 mg/28.5 mg and Amoxicillin and Clavulanate Potassium 400 mg/57 mg chewable tablets contain aspartame and should not be used by phenylketonurics. [see Warnings and Precautions (5.8)].

Table 3: Dosing in Patients Aged 12 Weeks (3 Months) and Older and Weighing Less than 40 kg

Patients Weighing 40 kg or More: Pediatric patients weighing 40 kg or more should be dosed according to adult recommendations.

- The 250 mg/125 mg tablet of AUGMENTIN should NOT be used until the child weighs at least 40 kg, due to the different amoxicillin to clavulanic acid ratios in the 250 mg/125 mg tablet of AUGMENTIN versus the 250 mg/62.5 mg chewable tablet of AUGMENTIN.

2.4 Patients with Renal Impairment

Patients with impaired renal function do not generally require a reduction in dose unless the impairment is severe. Renal impairment patients with a glomerular filtration rate (GFR) of less than 30 mL/min should NOT receive the 875 mg dose (based on the amoxicillin component) of AUGMENTIN. See dosing regimens in patients with severe renal impairment provided in Table 4.

Table 4. Dosing Regimens of AUGMENTIN in Patients with Severe Renal Impairment

Patients with Renal Impairment | Dosing Regimen
GFR 10 mL/min to 30 mL/min | 500 mg or 250 mg every 12 hours, depending; on the severity of the infection
GFR less than 10 mL/min | 500 mg or 250 mg every 24 hours, depending; on severity of the infection
Hemodialysis | 500 mg or 250 mg every 24 hours, depending; on severity of the infection Administer an additional dose both during; and at the end of dialysis

2.5 Directions for Mixing Amoxicillin and Clavulanate Potassium for Oral Suspension

Prepare AUGMENTIN for oral suspension at time of dispensing as follows: Tap bottle until all powder flows freely. Measure a total (see Table 5 below for total amount of water for reconstitution) OF WATER. Add approximately 2/3 of the water to the powder. Replace cap and shake VIGOROUSLY. Add remaining water. Replace cap and shake VIGOROUSLY.

Table 5: Amount of Water for Mixing AUGMENTIN for Oral Suspension

Strength of AUGMENTIN Oral Suspension | Bottle Size | Amount of Water for Reconstitution | Contents of Each Teaspoonful (5 mL)
125 mg/31.25 mg; per 5 mL | 75 mL 100 mL 150 mL | 67 mL 90 mL 134 mL | 125 mg of amoxicillin and 31.25 mg of clavulanic acid as the potassium salt
250 mg/62.5 mg; per 5 mL | 75 mL 100 mL 150 mL | 65 mL 87 mL 130 mL | 250 mg of amoxicillin and 62.5 mg of clavulanic acid as the potassium salt

Shake oral suspension well before using. Reconstituted suspension must be stored under refrigeration and discarded after 10 days. Some color change is normal during dosing period.

2.6 Switching between Dosage Forms and between Strengths

AUGMENTIN 250 mg/125 mg Tablet is NOT Substitutable with AUGMENTIN 250 mg/62.5 mg Chewable Tablet

The 250 mg/125 mg tablet of AUGMENTIN and the 250 mg/62.5 mg chewable tablet of AUGMENTIN should NOT be substituted for each other and the 250 mg/125 mg tablet of AUGMENTIN should NOT be used in pediatric patients weighing less than 40 kg [see Dosage and Administration (2.3)] . The 250 mg tablet of AUGMENTIN and the 250 mg chewable tablet of AUGMENTIN do not contain the same amount of clavulanic acid. The 250 mg tablet of AUGMENTIN contains 125 mg of clavulanic acid whereas the 250 mg chewable tablet of AUGMENTIN contains 62.5 mg of clavulanic acid.

Two AUGMENTIN 250 mg/125 mg Tablets are NOT Substitutable with One 500 mg/125 mg AUGMENTIN Tablet

Two 250 mg/125 mg tablets of AUGMENTIN should NOT be substituted for one 500 mg/125 mg tablet of AUGMENTIN. Since both the 250 mg and 500 mg tablets of AUGMNTIN contain the same amount of clavulanic acid (125 mg, as the potassium salt), two 250 mg tablets of AUGMENTIN are not equivalent to one 500 mg tablet of AUGMENTIN.

3 DOSAGE FORMS AND STRENGTHS

Augmentin for Oral Suspension, USP:

- 125 mg/31.25 mg per 5 mL: Banana-flavored powder for oral suspension (each 5 mL of reconstituted suspension contains 125 mg of amoxicillin as the trihydrate and 31.25 mg of clavulanic acid as the potassium salt).
- 250 mg/62.5 mg per 5 mL: Orange-flavored powder for oral suspension (each 5 mL of reconstituted suspension contains 250 mg of amoxicillin as the trihydrate and 62.5 mg of clavulanic acid as the potassium salt).

4 CONTRAINDICATIONS

4.1 Serious Hypersensitivity Reactions

AUGMENTIN is contraindicated in patients with a history of serious hypersensitivity reactions (e.g., anaphylaxis or Stevens-Johnson syndrome) to amoxicillin, clavulanate or to other beta‑lactam antibacterial drugs (e.g., penicillins and cephalosporins).

4.2 Cholestatic Jaundice/Hepatic Dysfunction

AUGMENTIN is contraindicated in patients with a previous history of cholestatic jaundice/hepatic dysfunction associated with AUGMENTIN.

5 WARNINGS AND PRECAUTIONS

5.1 Hypersensitivity Reactions

Serious and occasionally fatal hypersensitivity (anaphylactic) reactions have been reported in patients receiving beta-lactam antibacterials, including AUGMENTIN. These reactions are more likely to occur in individuals with a history of penicillin hypersensitivity and/or a history of sensitivity to multiple allergens. Before initiating therapy with AUGMENTIN, careful inquiry should be made regarding previous hypersensitivity reactions to penicillins, cephalosporins, or other allergens. If an allergic reaction occurs, AUGMENTIN should be discontinued, and appropriate therapy instituted.

5.2 Severe Cutaneous Adverse Reactions

AUGMENTIN may cause severe cutaneous adverse reactions (SCAR), such as Stevens-Johnson syndrome (SJS), toxic epidermal necrolysis (TEN), drug reaction with eosinophilia and systemic symptoms (DRESS), and acute generalized exanthematous pustulosis (AGEP). If patients develop a skin rash, they should be monitored closely, and AUGMENTIN discontinued if lesions progress.

5.3 Drug-Induced Enterocolitis Syndrome (DIES)

Drug-induced enterocolitis syndrome (DIES) has been reported with use of amoxicillin, a componet of AUGMENTIN

[see Adverse Reactions (6.2)], with most cases occurring in pediatric patients < 18 years of age. DIES is a non IgE mediated

hypersensitivity reaction characterized by protracted vomiting occuring 1 to 4 hours after drug ingestion in the absence of

skin or respiratory symptoms. DIES may be associated with pallor, lethargy, hypotension, shock, diarrhea within 24 hours of ingesting

amoxicillin, and leukocytosis with neutrophilia. If DIES occurs, discontinue AUGMENTIN and institute appropriate therapy.

5.4 Hepatic Dysfunction

Hepatic dysfunction, including hepatitis and cholestatic jaundice has been associated with the use of AUGMENTIN. Hepatic toxicity is usually reversible; however, deaths have been reported. Hepatic function should be monitored at regular intervals in patients with hepatic impairment.

5.5 Clostridioides difficile Associated Diarrhea (CDAD)

Clostridioides difficile associated diarrhea (CDAD) has been reported with use of nearly all antibacterial agents, including AUGMENTIN, and may range in severity from mild diarrhea to fatal colitis. Treatment with antibacterial agents alters the normal flora of the colon leading to overgrowth of C. difficile.

C. difficile produces toxins A and B which contribute to the development of CDAD. Hypertoxin-producing strains of C. difficile cause increased morbidity and mortality, as these infections can be refractory to antimicrobial therapy and may require colectomy. CDAD must be considered in all patients who present with diarrhea following antibacterial use. Careful medical history is necessary since CDAD has been reported to occur over 2 months after the administration of antibacterial agents.

If CDAD is suspected or confirmed, ongoing antibacterial use not directed against C. difficile may need to be discontinued. Appropriate fluid and electrolyte management, protein supplementation, antibacterial treatment of C. difficile, and surgical evaluation should be instituted as clinically indicated.

5.6 Skin Rash in Patients with Mononucleosis

A high percentage of patients with mononucleosis who receive amoxicillin develop an erythematous skin rash. Thus, AUGMENTIN should not be administered to patients with mononucleosis.

5.7 Potential for Microbial Overgrowth

The possibility of superinfections with fungal or bacterial pathogens should be considered during therapy. If superinfection occurs, amoxicillin and clavulanate potassium should be discontinued and appropriate therapy instituted.

5.8 Phenylketonurics

AUGMENTIN Chewable tablets and AUGMENTIN for Oral Suspension contain aspartame which contains phenylalanine. Each 200 mg chewable tablet of AUGMENTIN contains 2.1 mg phenylalanine; each 400 mg chewable tablet contains 4.2 mg phenylalanine; each 5 mL of either the 200 mg/5 mL or 400 mg/5 mL oral suspension contains 7 mg phenylalanine. The other formulations of AUGMENTIN do not contain phenylalanine.

5.9 Development of Drug-Resistant Bacteria

Prescribing AUGMENTIN in the absence of a proven or strongly suspected bacterial infection or a prophylactic indication is unlikely to provide benefit to the patient and increases the risk of the development of drug‑resistant bacteria.

6 ADVERSE REACTIONS

The following are discussed in more detail in other sections of the labeling:

- Anaphylactic reactions [see Warnings and Precautions (5.1)]
- Severe Cutaneous Adverse Reactions [see Warnings and Precautions (5.2)]
- Drug-Induced Enterocolitis Syndrom (DIES) [see Warnings and Precautions (5.3)]
- Hepatic Dysfunction [see Warnings and Precautions (5.4]
- Clostridioides difficile Associated Diarrhea (CDAD) [see Warnings and Precautions (5.5]

6.1 Clinical Trial Experience

Because clinical trials are conducted under widely varying conditions, adverse reaction rates observed in the clinical trials of a drug cannot be directly compared to rates in the clinical trials of another drug and may not reflect the rates observed in practice.

The most frequently reported adverse reactions were diarrhea/loose stools (9%), nausea (3%), skin rashes and urticaria (3%), vomiting (1%) and vaginitis (1%). Less than 3% of patients discontinued therapy because of drug‑related adverse reactions. The overall incidence of adverse reactions, and in particular diarrhea, increased with the higher recommended dose. Other less frequently reported adverse reactions (less than 1%) include: Abdominal discomfort, flatulence, and headache.

In pediatric patients (aged 2 months to 12 years), 1 US/Canadian clinical trial was conducted which compared 45/6.4 mg/kg/day (divided every 12 hours) of Amoxicillin and Clavulanate Potassium for 10 days versus 40/10 mg/kg/day (divided every 8 hours) of Amoxicillin and Clavulanate Potassium for 10 days in the treatment of acute otitis media. A total of 575 patients were enrolled, and only the suspension formulations were used in this trial. Overall, the adverse reactions seen were comparable to that noted above; however, there were differences in the rates of diarrhea, skin rashes/urticaria, and diaper area rashes. [see Clinical Studies (14.2)] .

6.2 Postmarketing Experience

In addition to adverse reactions reported from clinical trials, the following have been identified during postmarketing use of AUGMENTIN. Because they are reported voluntarily from a population of unknown size, estimates of frequency cannot be made. These events have been chosen for inclusion due to a combination of their seriousness, frequency of reporting, or potential causal connection to Amoxicillin and Clavulanate Potassium.

Gastrointestinal: Drug-induced enterocolitis syndrome (DIES), indigestion, gastritis, stomatitis, glossitis, black “hairy” tongue, mucocutaneous candidiasis, enterocolitis, and hemorrhagic/pseudomembranous colitis. Onset of pseudomembranous colitis symptoms may occur during or after antibacterial treatment. [see Warnings and Precautions (5.5] .

Immune: Hypersensitivity reactions, anaphylactic/anaphylactoid reactions (including shock), angioedema, serum sickness-like reactions (urticaria or skin rash accompanied by arthritis, arthralgia, myalgia, and frequently fever), hypersensitivity vasculitis [see Warnings and Precautions (5.1)] .

Skin and Appendages: Rashes, pruritus, urticaria, erythema multiforme, SJS, TEN, DRESS, AGEP, exfoliative dermatitis , and linear IgA dermatosis.

Liver: Hepatic dysfunction, including hepatitis and cholestatic jaundice, increases in serum transaminases (AST and/or ALT), serum bilirubin, and/or alkaline phosphatase, has been reported with Amoxicillin and Clavulanate Potassium. It has been reported more commonly in the elderly, in males, or in patients on prolonged treatment. The histologic findings on liver biopsy have consisted of predominantly cholestatic, hepatocellular, or mixed cholestatic hepatocellular changes. The onset of signs/symptoms of hepatic dysfunction may occur during or several weeks after therapy has been discontinued. The hepatic dysfunction, which may be severe, is usually reversible. Deaths have been reported [see Contraindications (4.2), Warnings and Precautions (5.4)] .

Renal: Interstitial nephritis, hematuria, and crystalluria have been reported [see Overdosage (10)] .

Hemic and Lymphatic Systems: Anemia, including hemolytic anemia, thrombocytopenia, thrombocytopenic purpura, eosinophilia, leukopenia, and agranulocytosis have been reported. These reactions are usually reversible on discontinuation of therapy and are believed to be hypersensitivity phenomena. Thrombocytosis was noted in less than 1% of the patients treated with AUGMENTIN. There have been reports of increased prothrombin time in patients receiving AUGMENTIN and anticoagulant therapy concomitantly [see Drug Interactions (7.2)] .

Central Nervous System: Agitation, anxiety, behavioral changes, aseptic meningitis, confusion, convulsions, dizziness, insomnia, and reversible hyperactivity have been reported.

Miscellaneous: Tooth discoloration (brown, yellow, or gray staining) has been reported. Most reports occurred in pediatric patients. Discoloration was reduced or eliminated with brushing or dental cleaning in most cases.

7 DRUG INTERACTIONS

7.1 Probenecid

Probenecid decreases the renal tubular secretion of amoxicillin but does not delay renal excretion of clavulanic acid. Concurrent use with AUGMENTIN may result in increased and prolonged blood concentrations of amoxicillin. Co-administration of probenecid is not recommended.

7.2 Oral Anticoagulants

Abnormal prolongation of prothrombin time (increased international normalized ratio [INR]) has been reported in patients receiving amoxicillin and oral anticoagulants. Appropriate monitoring should be undertaken when anticoagulants are prescribed concurrently with AUGMENTIN. Adjustments in the dose of oral anticoagulants may be necessary to maintain the desired level of anticoagulation.

7.3 Allopurinol

The concurrent administration of allopurinol and amoxicillin increases the incidence of rashes in patients receiving both drugs as compared to patients receiving amoxicillin alone. It is not known whether this potentiation of amoxicillin rashes is due to allopurinol or the hyperuricemia present in these patients.

7.4 Oral Contraceptives

AUGMENTIN may affect intestinal flora, leading to lower estrogen reabsorption and reduced efficacy of combined oral estrogen/progesterone contraceptives.

7.5 Effects on Laboratory Tests

High urine concentrations of amoxicillin may result in false-positive reactions when testing for the presence of glucose in urine using CLINITEST®, Benedict's Solution, or Fehling's Solution. Since this effect may also occur with AUGMENTIN, it is recommended that glucose tests based on enzymatic glucose oxidase reactions be used.

Following administration of amoxicillin to pregnant women, a transient decrease in plasma concentration of total conjugated estriol, estriol-glucuronide, conjugated estrone, and estradiol has been noted.

8 USE IN SPECIFIC POPULATIONS

8.1 Pregnancy

TERATOGENIC EFFECTS

Teratogenic Effects: Pregnancy Category B. Reproduction studies performed in pregnant rats and mice given AUGMENTIN (2:1 ratio formulation of amoxicillin:clavulanate) at oral doses up to 1200 mg/kg/day revealed no evidence of harm to the fetus due to AUGMENTIN. The amoxicillin doses in rats and mice (based on body surface area) were approximately 4 and 2 times the maximum recommended adult human oral dose (875 mg every 12 hours). For clavulanate, these dose multiples were approximately 9 and 4 times the maximum recommended adult human oral dose (125 mg every 8 hours). There are, however, no adequate and well-controlled studies in pregnant women. Because animal reproduction studies are not always predictive of human response, this drug should be used during pregnancy only if clearly needed.

8.2 Labor and Delivery

Oral ampicillin‑class antibacterials are poorly absorbed during labor. It is not known whether use of amoxicillin and clavulanate potassium in humans during labor or delivery has immediate or delayed adverse effects on the fetus, prolongs the duration of labor, or increases the likelihood of the necessity for an obstetrical intervention.

8.3 Nursing Mothers

Amoxicillin has been shown to be excreted in human milk. Amoxicillin and clavulanate potassium use by nursing mothers may lead to sensitization of infants. Caution should be exercised when amoxicillin and clavulanate potassium is administered to a nursing woman.

8.4 Pediatric Use

The safety and effectiveness of AUGMENTIN for Oral Suspension and Chewable Tablets have been established in pediatric patients. Use of AUGMENTIN in pediatric patients is supported by evidence from studies of AUGMENTIN Tablets in adults with additional data from a study of AUGMENTIN for Oral Suspension in pediatric patients aged 2 months to 12 years with acute otitis media [see Clinical Studies (14.2)] .

Because of incompletely developed renal function in neonates and young infants, the elimination of amoxicillin may be delayed; clavulanate elimination is unaltered in this age group. Dosing of Amoxicillin and Clavulanate Potassium should be modified in pediatric patients aged less than 12 weeks (less than 3 months) [see Dosage and Administration (2.3)].

8.5 Geriatric Use

Of the 3,119 patients in an analysis of clinical studies of AUGMENTIN, 32% were greater than or equal to 65 years old, and 14% were greater than or equal to 75 years old. No overall differences in safety or effectiveness were observed between these subjects and younger subjects, and other reported clinical experience has not identified differences in responses between the elderly and younger patients, but greater sensitivity of some older individuals cannot be ruled out.

This drug is known to be substantially excreted by the kidney, and the risk of adverse reactions to this drug may be greater in patients with impaired renal function. Because elderly patients are more likely to have decreased renal function, care should be taken in dose selection, and it may be useful to monitor renal function.

8.6 Renal Impairment

Amoxicillin is primarily eliminated by the kidney and dosage adjustment is usually required in patients with severe renal impairment (GFR less than 30 mL/min). See Patients with Renal Impairment [see Dosage and Administration (2.4)] for specific recommendations in patients with renal impairment.

10 OVERDOSAGE

In case of overdosage, discontinue medication, treat symptomatically, and institute supportive measures as required. A prospective study of 51 pediatric patients at a poison-control center suggested that overdosages of less than 250 mg/kg of amoxicillin are not associated with significant clinical symptoms^1.

Interstitial nephritis resulting in oliguric renal failure has been reported in patients after overdosage with amoxicillin and clavulanate potassium.

Crystalluria, in some cases leading to renal failure, has also been reported after amoxicillin and clavulanate potassium overdosage in adult and pediatric patients. In case of overdosage, adequate fluid intake and diuresis should be maintained to reduce the risk of amoxicillin and clavulanate potassium crystalluria.

Renal impairment appears to be reversible with cessation of drug administration. High blood levels may occur more readily in patients with impaired renal function because of decreased renal clearance of amoxicillin and clavulanate potassium. Amoxicillin and clavulanate potassium may be removed from circulation by hemodialysis [see Dosage and Administration (2.4)] .

11 DESCRIPTION

AUGMENTIN is an oral antibacterial combination consisting of amoxicillin and the beta‑lactamase inhibitor, clavulanate potassium (the potassium salt of clavulanic acid).

Amoxicillin is an analog of ampicillin, derived from the basic penicillin nucleus, 6‑aminopenicillanic acid. The amoxicillin molecular formula is C16H19N3O5S•3H2O, and the molecular weight is 419.46. Chemically, amoxicillin is (2 S,5 R,6 R)-6-[(R)-(-)-2-Amino-2-(p-hydroxyphenyl)acetamido]-3,3-dimethyl-7-oxo-4-thia-1-azabicyclo[3.2.0]heptane-2-carboxylic acid trihydrate and may be represented structurally as:

Clavulanic acid is produced by the fermentation of Streptomyces clavuligerus. It is a beta-lactam structurally related to the penicillins and possesses the ability to inactivate some beta‑lactamases by blocking the active sites of these enzymes. The clavulanate potassium molecular formula is C8H8KNO5, and the molecular weight is 237.25. Chemically, clavulanate potassium is potassium (Z)(2 R,5 R)-3-(2-hydroxyethylidene)-7-oxo-4-oxa-1-azabicyclo[3.2.0]-heptane-2-carboxylate and may be represented structurally as:

AUGMENTIN for Oral Suspension:

- 125 mg/31.25 mg: Following constitution, each 5 mL of oral suspension contains 125 mg of amoxicillin as the trihydrate, and 31.25 mg of clavulanic acid (equivalent to 37.23 mg of clavulanate potassium).
- 250 mg/62.5 mg: Following constitution, each 5 mL of oral suspension contains 250 mg of amoxicillin as the trihydrate, and 62.5 mg of clavulanic acid (equivalent to 74.5 mg of clavulanate potassium).

Inactive Ingredients:

- AUGMENTIN for Oral Suspension, 125 mg/31.5 mg per 5mL and 250 mg/62.5 mg per 5mL - Colloidal silicon dioxide, flavorings, xanthan gum, mannitol, succinic acid, silica gel and sodium saccharin.
  • Each 5 mL of reconstituted 125 mg/31.5 mg oral suspension of AUGMENTIN contains 0.16 mEq potassium
  • Each 5 mL of reconstituted 250 mg/62.5 mg oral suspension of AUGMENTIN contains 0.32 mEq potassium

12 CLINICAL PHARMACOLOGY

12.1 Mechanism of Action

AUGMENTIN is an antibacterial drug [see Microbiology (12.4)] .

12.3 Pharmacokinetics

Mean amoxicillin and clavulanate potassium pharmacokinetic parameters in normal adults following administration of Amoxicillin and Clavulanate Potassium Tablets are shown in Table 6 and following administration of Amoxicillin and Clavulanate Potassium for Oral Suspension and Chewable Tablets are shown in Table 7.

Table 6: Mean (±S.D.) Amoxicillin and Clavulanate Potassium Pharmacokinetic Parameters a,b with Amoxicillin and Clavulanate Potassium Tablets

Table 7: Mean (±S.D.) Amoxicillin and Clavulanate Potassium Pharmacokinetic Parameters a,b with Amoxicillin and Clavulanate Potassium for Oral Suspension and Chewable Tablets

Oral administration of 5 mL of the 250 mg/62.5 mg suspension of Amoxicillin and Clavulanate Potassium or the equivalent dose of 10 mL of the 125 mg/31.25 mg suspension of Amoxicillin and Clavulanate Potassium provides average peak serum concentrations approximately 1 hour after dosing of 6.9 mcg/mL for amoxicillin and 1.6 mcg/mL for clavulanic acid. The areas under the serum concentration curves obtained during the first 4 hours after dosing were 12.6 mcg*h/mL for amoxicillin and 2.9 mcg*h/mL for clavulanic acid when 5 mL of the 250 mg/62.5 mg suspension of Amoxicillin and Clavulanate Potassium or equivalent dose of 10 mL of the 125 mg/31.25 mg suspension of Amoxicillin and Clavulanate Potassium were administered to normal adults. One 250 mg/62.5 mg chewable tablet of Amoxicillin and Clavulanate Potassium or two 125 mg/31.25 mg chewable tablets of Amoxicillin and Clavulanate Potassium are equivalent to 5 mL of the 250 mg/62.5 mg suspension of Amoxicillin and Clavulanate Potassium and provide similar serum concentrations of amoxicillin and clavulanic acid.

Amoxicillin serum concentrations achieved with Amoxicillin and Clavulanate Potassium are similar to those produced by the oral administration of equivalent doses of amoxicillin alone. Time above the minimum inhibitory concentration of 1 mcg/mL for amoxicillin has been shown to be similar after corresponding every 12 hour and every 8-hour dosing regimens of Amoxicillin and Clavulanate Potassium in adults and children.

Absorption: Dosing in the fasted or fed state has minimal effect on the pharmacokinetics of amoxicillin. While AUGMENTIN can be given without regard to meals, absorption of clavulanate potassium when taken with food is greater relative to the fasted state. In one study, the relative bioavailability of clavulanate was reduced when AUGMENTIN was dosed at 30 and 150 minutes after the start of a high‑fat breakfast.

Distribution: Neither component in AUGMENTIN is highly protein‑bound; clavulanic acid is approximately 25% bound to human serum and amoxicillin approximately 18% bound

Amoxicillin diffuses readily into most body tissues and fluids with the exception of the brain and spinal fluid.

Two hours after oral administration of a single 35 mg/kg dose of suspension of AUGMENTIN to fasting children, average concentrations of 3 mcg/mL of amoxicillin and 0.5 mcg/mL of clavulanic acid were detected in middle ear effusions.

Metabolism and Excretion: The half‑life of amoxicillin after the oral administration of AUGMENTIN is 1.3 hours and that of clavulanic acid is 1 hour.

Approximately 50% to 70% of the amoxicillin and approximately 25% to 40% of the clavulanic acid are excreted unchanged in urine during the first 6 hours after administration of a single 250 mg/125 mg or 500 mg/125 mg tablet of AUGMENTIN.

12.4 Microbiology

Amoxicillin is a semisynthetic antibacterial with in vitro bactericidal activity against Gram-positive and Gram-negative bacteria. Amoxicillin is, however, susceptible to degradation by beta-lactamases, and therefore, the spectrum of activity does not include organisms which produce these enzymes. Clavulanic acid is a beta-lactam, structurally related to the penicillins, which possesses the ability to inactivate some beta-lactamase enzymes commonly found in microorganisms resistant to penicillins and cephalosporins. In particular, it has good activity against the clinically important plasmid-mediated beta-lactamases frequently responsible for transferred drug resistance.

The formulation of amoxicillin and clavulanic acid in AUGMENTIN protects amoxicillin from degradation by some beta-lactamase enzymes and extends the antibacterial spectrum of amoxicillin to include many bacteria normally resistant to amoxicillin.

Amoxicillin and clavulanic acid has been shown to be active against most isolates of the following bacteria, both in vitro and in clinical infections [see Indications and Usage (1)] .

Gram-positive bacteria

Staphylococcus aureus

Gram-negative bacteria

Enterobacter species

Escherichia coli

Haemophilus influenzae

Klebsiella species

Moraxella catarrhalis

The following in vitro data are available, but their clinical significance is unknown. At least 90 percent of the following bacteria exhibit an in vitro minimum inhibitory concentration (MIC) less than or equal to the susceptible breakpoint for amoxicillin and clavulanic acid. However, the efficacy of amoxicillin and clavulanic acid in treating clinical infections due to these bacteria has not been established in adequate and well-controlled clinical trials.

Gram-positive bacteria

Enterococcus faecalis

Staphylococcus epidermidis

Staphylococcus saprophyticus

Streptococcus pneumoniae

Streptococcus pyogenes

Viridans group Streptococcus

Gram-negative Bacteria

Eikenella corrodens

Proteus mirabilis

Anaerobic Bacteria

Bacteroides species including Bacteroides fragilis

Fusobacterium species

Peptostreptococcus species

Susceptibility Test Methods

For specific information regarding susceptibility test interpretive criteria and associated test methods and quality control standards recognized by FDA for this drug, please see: https://www.fda.gov/STIC.

13 NONCLINICAL TOXICOLOGY

13.1 Carcinogenesis, Mutagenesis, Impairment of Fertility

Long‑term studies in animals have not been performed to evaluate carcinogenic potential.

AUGMENTIN (4:1 ratio formulation of amoxicillin:clavulanate) was non-mutagenic in the Ames bacterial mutation assay, and the yeast gene conversion assay. AUGMENTIN was weakly positive in the mouse lymphoma assay, but the trend toward increased mutation frequencies in this assay occurred at doses that were also associated with decreased cell survival. AUGMENTING was negative in the mouse micronucleus test, and in the dominant lethal assay in mice. Potassium clavulanate alone was tested in the Ames bacterial mutation assay and in the mouse micronucleus test, and was negative in each of these assays.

AUGMENTIN (2:1 ratio formulation of amoxicillin:clavulanate) at oral doses of up to 1,200 mg/kg/day was found to have no effect on fertility and reproductive performance in rats. Based on body surface area, this dose of amoxicillin is approximately 4 times the maximum recommended adult human oral dose (875 mg every 12 hours). For clavulanate, the dose multiple is approximately 9 times higher than the maximum recommended adult human oral dose (125 mg every 8 hours), also based on body surface area.

14 CLINICAL STUDIES

14.1 Lower Respiratory Tract and Complicated Urinary Tract Infections

Data from 2 pivotal trials in 1,191 patients treated for either lower respiratory tract infections or complicated urinary tract infections compared a regimen of 875 mg/125 mg tablets of Amoxicillin and Clavulanate Potassium every 12 hours to 500 mg/125 mg tablets of Amoxicillin and Clavulanate Potassium dosed every 8 hours (584 and 607 patients, respectively). Comparable efficacy was demonstrated between the every 12 hours and every 8 hours dosing regimens. There was no significant difference in the percentage of adverse events in each group. The most frequently reported adverse event was diarrhea; incidence rates were similar for the 875 mg/125 mg every 12 hours and 500 mg/125 mg every 8 hours dosing regimens (15% and 14%, respectively); however, there was a statistically significant difference (p less than 0.05) in rates of severe diarrhea or withdrawals with diarrhea between the regimens: 1% for 875 mg/125 mg every 12 hours regimen versus 2% for the 500 mg/125 mg every 8 hours regimen.

In one of these pivotal trials, patients with either pyelonephritis (n equals 361) or a complicated urinary tract infection (i.e., patients with abnormalities of the urinary tract that predispose to relapse of bacteriuria following eradication, n equals 268) were randomized (1:1) to receive either 875 mg/125mg tablets of AUGMENTIN every 12 hours (n equals 308) or 500 mg/125 mg tablets of AUGMENTIN every 8 hours (n equals 321).

The number of bacteriologically evaluable patients was comparable between the two dosing regimens. AUGMENTIN produced comparable bacteriological success rates in patients assessed 2 to 4 days immediately following end of therapy. The bacteriologic efficacy rates were comparable at one of the follow‑up visits (5 to 9 days post‑therapy) and at a late post‑therapy visit (in the majority of cases, this was 2 to 4 weeks post-therapy), as seen in Table 8.

Table 8: Bacteriologic efficacy rates for AUGMENTIN

Time Post Therapy | 875 mg every 12 hours % (n) | 500 mg every 8 hours % (n)
2 to 4 days | 81% (58) | 80% (54)
5 to 9 days | 58% (41) | 52% (52)
2 to 4 weeks | 52% (101) | 55% (104)

As noted before, though there was no significant difference in the percentage of adverse events in each group, there was a statistically significant difference in rates of severe diarrhea or withdrawals with diarrhea between the regimens.

14.2 Acute Bacterial Otitis Media and Diarrhea in Pediatric Patients

One US/Canadian clinical trial was conducted which compared 45/6.4 mg/kg/day (divided every 12 hours) of AUGMENTIN for 10 days versus 40/10 mg/kg/day (divided every 8 hours) of AUGMENTIN for 10 days in the treatment of acute otitis media. Only the suspension formulations were used in this trial. A total of 575 pediatric patients (aged 2 months to 12 years) were enrolled, with an even distribution among the 2 treatment groups and a comparable number of patients were evaluable (i.e., greater than or equal to 84%) per treatment group. Otitis media‑specific criteria were required for eligibility and a strong correlation was found at the end of therapy and follow‑up between these criteria and physician assessment of clinical response. The clinical efficacy rates at the end of therapy visit (defined as 2 to 4 days after the completion of therapy) and at the follow‑up visit (defined as 22 to 28 days post‑completion of therapy) were comparable for the 2 treatment groups, with the following cure rates obtained for the evaluable patients: At end of therapy, 87% (n equals 265) and 82% (n equals 260) for 45 mg/kg/day every 12 hours and 40 mg/kg/day every 8 hours, respectively. At follow‑up, 67% (n equals 249) and 69% (n equals 243) for 45 mg/kg/day every 12 hours and 40 mg/kg/day every 8 hours, respectively.

Diarrhea was defined as either: (a) 3 or more watery or 4 or more loose/watery stools in 1 day; OR (b) 2 watery stools per day or 3 loose/watery stools per day for 2 consecutive days. The incidence of diarrhea was significantly lower in patients who received the every 12 hours regimen compared to patients who received the every 8 hours regimen (14% and 34%, respectively). In addition, the number of patients with either severe diarrhea or who were withdrawn with diarrhea was significantly lower in the every 12 hours treatment group (3% and 8% for the every 12 hours/10 day and every 8 hours/10 day, respectively). In the every 12 hours treatment group, 3 patients (1%) were withdrawn with an allergic reaction, while 1 patient in the every 8 hours group was withdrawn for this reason. The number of patients with a candidal infection of the diaper area was 4% and 6% for the every 12 hours and every 8 hours groups, respectively.

It is not known if the finding of a statistically significant reduction in diarrhea with the oral suspensions dosed every 12 hours, versus suspensions dosed every 8 hours of AUGMENTIN, can be extrapolated to the chewable tablets. The presence of mannitol in the chewable tablets of AUGMENTIN may contribute to a different diarrhea profile. The every 12 hour oral suspensions (200 mg/28.5 mg per 5 mL and 400 mg/57 mg per 5 mL) of AUGMENTIN are sweetened with aspartame.

15 REFERENCES

1. Swanson-Biearman B, Dean BS, Lopez G, Krenzelok EP. The effects of penicillin and cephalosporin ingestions in children less than six years of age. Vet Hum Toxicol. 1988; 30: 66‑67.

16 HOW SUPPLIED/STORAGE AND HANDLING

AUGMENTIN for Oral Suspension, USP:

125 mg/31.25 mg per 5 mL: Banana-flavored powder for oral suspension, each 5 mL of reconstituted suspension contains 125 mg of amoxicillin as the trihydrate and 31.25 mg of clavulanic acid as the potassium salt (equivalent to 37.23 mg of clavulanate potassium).

NDC71297-240-34 | 75 mL bottle
NDC 71297-240-35 | 100 mL bottle
NDC 71297-240-36 | 150 mL bottle

Dispense in original container.

Store dry powder at or below 25°C (77°F).

Store reconstituted suspension under refrigeration. Discard unused suspension after 10 days.

Keep out of the reach of children.

17 PATIENT COUNSELING INFORMATION

Administration Instructions

Inform patients that AUGMENTIN may be taken every 8 hours or every 12 hours, depending on the dose prescribed. Each dose should be taken with a meal or snack to reduce the possibility of gastrointestinal upset.

Allergic Reactions

Counsel patients that AUGMENTIN contains a penicillin class drug product that can cause allergic reactions in some individuals.

Severe Cutaneous Adverse Reactions (SCAR)

Advise patients about the signs and symptoms of serious skin manifestations. Instruct patients to stop taking AUGMENTIN immediately and promptly report the first signs or symptoms of skin rash, mucosal lesions, or any other sign of hypersensitivity [see Warnings and Precautions (5.2)] .

Diarrhea

Counsel patients that diarrhea is a common problem caused by antibacterials, and it usually ends when the antibacterial is discontinued. Sometimes after starting treatment with antibacterials, patients can develop watery and bloody stools (with or without stomach cramps and fever) even as late as 2 or more months after having taken their last dose of the antibacterial. If diarrhea is severe or lasts more than 2 or 3 days, patients should contact their physician as soon as possible.

Antibacterial Resistance

Patients should be counseled that antibacterial drugs, including AUGMENTIN, should only be used to treat bacterial infections. They do not treat viral infections (e.g., the common cold).

When AUGMENTIN is prescribed to treat a bacterial infection, patients should be told that although it is common to feel better early in the course of therapy, the medication should be taken exactly as directed. Skipping doses or not completing the full course of therapy may: (1) decrease the effectiveness of the immediate treatment, and (2) increase the likelihood that bacteria will develop resistance and will not be treatable by AUGMENTIN or other antibacterial drugs in the future.

Storage Instructions

Advise patients to keep suspension refrigerated. Shake well before using. When dosing a child with the suspension (liquid) of AUGMENTIN, use a calibrated oral syringe. Be sure to rinse the calibrated oral syringe after each use. Bottles of suspension of AUGMENTIN may contain more liquid than required. Follow your doctor's instructions about the amount to use and the days of treatment your child requires. Discard any unused medicine.

Manufactured For:

Allegis Holdings, LLC
Canton, MS 39046 (USA)

Made in USA

AUGMENTIN is a registered trademark of GlaxoSmithKline and is sub-licensed to Allegis Holdings, LLC.
CLINITEST is a registered trademark of Miles, Inc.

Bottle Label (100 mL) 125mg/31.25mg for Oral Suspension

NDC 71297- 240-35

125 mg/31.25 mg per 5 mL

AUGMENTIN for oral suspension, USP

When reconstituted, each 5 mL contains:

AMOXICILLIN, 125 mgas the trihydrate, and

CLAVULANIC ACID, 31.25 mg(equivalent to 37.23 mg of clavulanate potassium)

100 mL(when reconstituted)

Rx only

Bottle Label (150 mL) 125mg/31.25mg for Oral Suspension

NDC 71297-240-36

125 mg/31.25 mg per 5 mL

AUGMENTIN for oral suspension, USP

When reconstituted, each 5 mL contains:

AMOXICILLIN, 125 mgas the trihydrate, and

CLAVULANIC ACID, 31.25 mg(equivalent to 37.23 mg of clavulanate potassium)

150 mL (when reconstituted)
Rx only

Bottle Label (75 mL) 125mg/31.25mg for Oral Suspension

NDC 71297- 240-34

125 mg/31.25 mg per 5 mL

AUGMENTIN for oral suspension, USP

When reconstituted, each 5 mL contains:

AMOXICILLIN, 125 mg as the trihydrate, and

CLAVULANIC ACID, 31.25 mg (equivalent to 37.23 mg of clavulanate potassium)

75 mL(when reconstituted)

Rx only